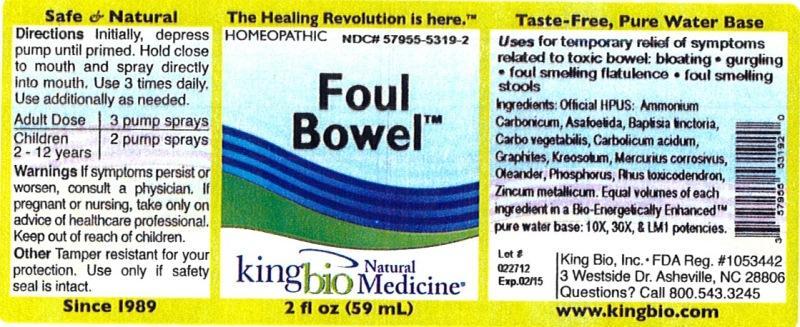 DRUG LABEL: Foul Bowel
NDC: 57955-5319 | Form: LIQUID
Manufacturer: King Bio Inc.
Category: homeopathic | Type: HUMAN OTC DRUG LABEL
Date: 20120719

ACTIVE INGREDIENTS: AMMONIUM CARBONATE 10 [hp_X]/59 mL; ASAFETIDA 10 [hp_X]/59 mL; BAPTISIA TINCTORIA ROOT 10 [hp_X]/59 mL; ACTIVATED CHARCOAL 10 [hp_X]/59 mL; PHENOL 10 [hp_X]/59 mL; GRAPHITE 10 [hp_X]/59 mL; WOOD CREOSOTE 10 [hp_X]/59 mL; MERCURIC CHLORIDE 10 [hp_X]/59 mL; NERIUM OLEANDER LEAF 10 [hp_X]/59 mL; PHOSPHORUS 10 [hp_X]/59 mL; TOXICODENDRON PUBESCENS LEAF 10 [hp_X]/59 mL; ZINC 10 [hp_X]/59 mL
INACTIVE INGREDIENTS: WATER

Foul Bowel

Active Ingredients

Official HPUS: Ammonium carbonicum, Asafoetida, Baptisia tinctoria, Carbo vegetabilis, Carbolicum acidum, Graphites, Kreosotum, Mercurius corrosivus, Oleander, Phosphorus, Rhus toxicodendron and Zincum metallicum

Inactive Ingredient

Equal volumes of each ingredient in a Bio-Energetically Enhanced pure water base: 10X, 30X, and LM1 potencies.

Purpose

Uses for temporary relief of symptoms related to toxic bowel:

- bloating
- gurgling
- foul smelling flatulence
- foul smelling stools

Warnings

If symptoms persist or worsen, consult a physician. If pregnant or nursing, take only on advice of healthcare professional. Keep out of reach of children.

Other: Tamper resistant for your protection. Use only if safety seal is intact.

Keep out of reach of children.

Directions

Initially, depress pump until primed. Hold close to mouth and spray directly into mouth. Use 3 times daily. Use additionally as needed.
Adult Dose 3 pump sprays
Children 2-12 years 2 pump sprays

INDICATIONS AND USAGE

Uses for temporary relief of symptoms related to toxic bowel: bloating, gurgling, foul smelling flatulence, foul smelling stools.

PACKAGE LABEL

King Bio Inc.

3 Westside Drive

Asheville, NC 28806

Questions? Call 800.543.3245

www.kingbio.com